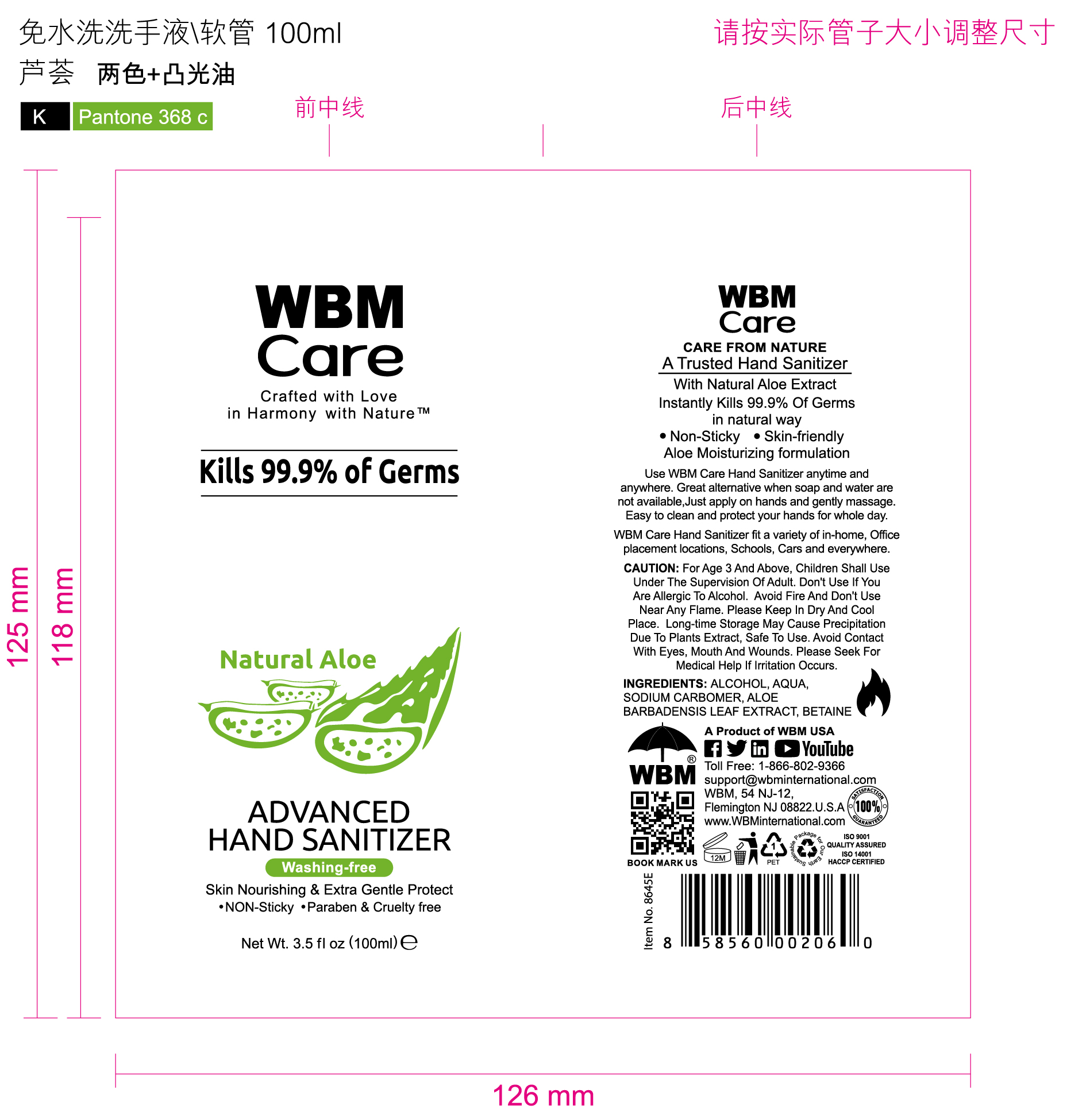 DRUG LABEL: ADVANCED HAND SANITIZER
NDC: 43116-007 | Form: GEL
Manufacturer: Shenzhen Shierjie Biological Engineering Co., LTD
Category: otc | Type: HUMAN OTC DRUG LABEL
Date: 20201122

ACTIVE INGREDIENTS: ALCOHOL 75 mL/100 mL
INACTIVE INGREDIENTS: BETAINE; CARBOMER HOMOPOLYMER, UNSPECIFIED TYPE; WATER; SODIUM; ALOE VERA LEAF

43116-007
ADVANCED HAND SANITIZER

Active Ingredient

Alcohol 75%

Purpose

/

Uses

Use WBM Care Hand Sanitizer anytime and anywhere.

Warnings

/

DO NOT USE

Don't Use If You Are Allergic To Alcohol. Avoid Fire And Don't Use Near Any Flame. Please Keep In Dry And Cool Place. Long-time Storage May Cause Precipitation Due To Plants Extract. Safe To Use. Avoid Contact With Eyes, Mouth And Wounds. Please Seek For Medical Help If Irritation Occurs.

WHEN USING

Great alternative when soap and water are not available.
Just apply on hands and gently massage. Easy to clean and protect your hands for whole day.
WBM Care Hand Sanitizer fit a variety of in-home, Office placement locations, Schools, Cars and everywhere

STOP USE

/

KEEP OUT OF REACH OF CHILDREN

/

Directions

/

Other information

/

Inactive ingredients

AQUA,SODIUM, CARBOMER,ALOE BARBADENSIS LEAF EXTRACT, BETAINE